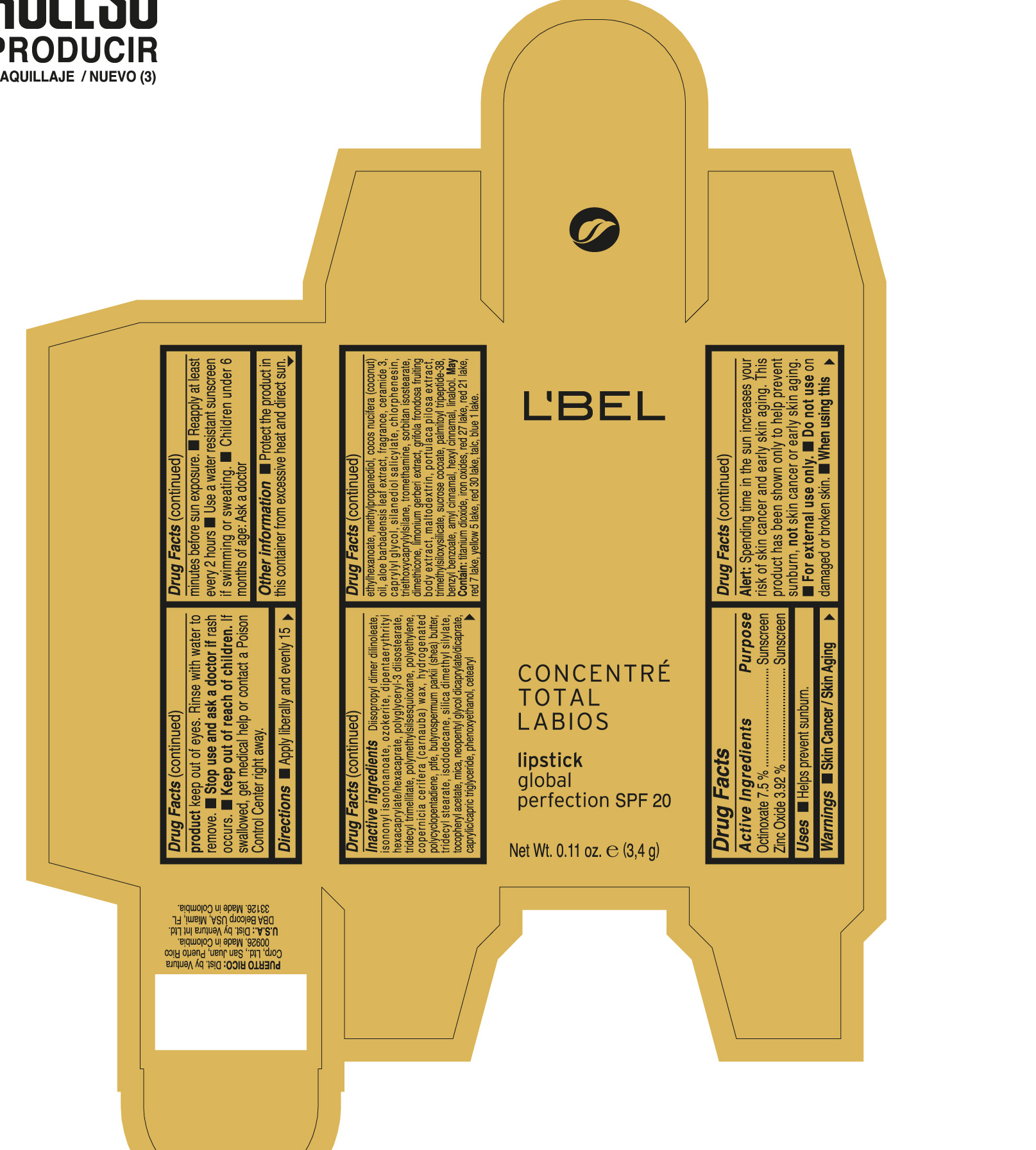 DRUG LABEL: LBEL CONCENTRE TOTAL LABIOS GLOBAL PERFECTION SPF 20
NDC: 14141-169 | Form: LIPSTICK
Manufacturer: Bel Star S.A. (Colombia)
Category: otc | Type: HUMAN OTC DRUG LABEL
Date: 20181121

ACTIVE INGREDIENTS: OCTINOXATE 0.075 g/1 g; ZINC OXIDE 0.0392 g/1 g
INACTIVE INGREDIENTS: DIISOPROPYL DILINOLEATE; ISONONYL ISONONANOATE; DIPENTAERYTHRITYL HEXACAPRYLATE/HEXACAPRATE; POLYGLYCERYL-3 DIISOSTEARATE; TRIDECYL TRIMELLITATE; POLYMETHYLSILSESQUIOXANE (4.5 MICRONS); HIGH DENSITY POLYETHYLENE; CARNAUBA WAX; POLYTETRAFLUOROETHYLENE; SHEA BUTTER; TRIDECYL STEARATE; ISODODECANE; SILICA DIMETHYL SILYLATE; MICA; NEOPENTYL GLYCOL DICAPRYLATE/DICAPRATE; MEDIUM-CHAIN TRIGLYCERIDES; PHENOXYETHANOL; CETEARYL ETHYLHEXANOATE; METHYLPROPANEDIOL; COCONUT OIL; ALOE VERA LEAF; CERAMIDE NP; CAPRYLYL GLYCOL; SILANEDIOL SALICYLATE; CHLORPHENESIN; TRIETHOXYCAPRYLYLSILANE; TROMETHAMINE; SORBITAN ISOSTEARATE; DIMETHICONE; MALTODEXTRIN; SUCROSE COCOATE; PALMITOYL LYSYLDIOXYMETHIONYLLYSINE; BENZYL BENZOATE; .ALPHA.-AMYLCINNAMALDEHYDE; .ALPHA.-HEXYLCINNAMALDEHYDE; LINALOOL, (+/-)-; TITANIUM DIOXIDE; FERRIC OXIDE RED; TALC

L'BEL CONCENTRÉ TOTAL LABIOS LIPSTICK GLOBAL PERFECTION SPF 20

Drug Facts

Active Ingredients | Purpose
OCTINOXATE 7.5 % | Sunscreen
ZINC OXIDE 3.92 % | Sunscreen

Uses

- Helps prevent sunburn.

Warnings

- Skin Cancer / Skin Aging Alert: Spending time in the sun increases your risk of skin cancer and early skin aging. This product has been shown only to help prevent sunburn, not skin cancer or early skin aging.

- For external use only.

- Do not use on damaged or broken skin.

- When using this product keep out of eyes. Rinse with water to remove.

- Stop use and ask a doctor if rash occurs.

Keep out of reach of children. If swallowed, get medical help or contact a Poison Control Center right away.

Directions

- Apply liberally and evenly 15 minutes before sun exposure.
- Reapply at least every 2 hours
- Use a water resistant sunscreen if swimming or sweating.
- Children under 6 months of age: Ask a doctor

Other information

- Protect the product in this container from excessive heat and direct sun.

Inactive ingredients

DIISOPROPYL DIMER DILINOLEATE, ISONONYL ISONONANOATE, OZOKERITE, DIPENTAERYTHRITYL HEXACAPRYLATE/HEXACAPRATE, POLYGLYCERYL-3 DIISOSTEARATE, TRIDECYL TRIMELLITATE, POLYMETHYLSILSESQUIOXANE, POLYETHYLENE, COPERNICIA CERIFERA (CARNAUBA) WAX, HYDROGENATED POLYCYCLOPENTADIENE, PTFE, BUTYROSPERMUM PARKII (SHEA) BUTTER, TRIDECYL STEARATE, ISODODECANE, SILICA DIMETHYL SILYLATE, TOCOPHERYL ACETATE, MICA, NEOPENTYL GLYCOL DICAPRYLATE/DICAPRATE, CAPRYLIC/CAPRIC TRIGLYCERIDE, PHENOXYETHANOL, CETEARYL ETHYLHEXANOATE, METHYLPROPANEDIOL, COCOS NUCIFERA (COCONUT) OIL, ALOE BARBADENSIS LEAF EXTRACT, FRAGRANCE, CERAMIDE 3, CAPRYLYL GLYCOL, SILANEDIOL SALICYLATE, CHLORPHENESIN, TRIETHOXYCAPRYLYLSILANE, TROMETHAMINE, SORBITAN ISOSTEARATE, DIMETHICONE, LIMONIUM GERBERI EXTRACT, GRIFOLA FRONDOSA FRUITING BODY EXTRACT, MALTODEXTRIN, PORTULACA PILOSA EXTRACT, TRIMETHYLSILOXYSILICATE, SUCROSE COCOATE, PALMITOYL TRIPEPTIDE-38, BENZYL BENZOATE, AMYL CINNAMAL, HEXYL CINNAMAL, LINALOOL. MAY CONTAIN : TITANIUM DIOXIDE, IRON OXIDES, RED 27 LAKE, RED 21 LAKE, RED 7 LAKE, YELLOW 5 LAKE, RED 30 LAKE, TALC, BLUE 1 LAKE.

Dist. by Ventura Int Ltd.
DBA Belcorp USA, Miami, FL
33126

PACKAGE LABEL

L'BEL

CONCENTRÉ
TOTAL
LABIOS

lipstick
global
perfection SPF 20

Net Wt. 0.11 oz. e (3,4 g)